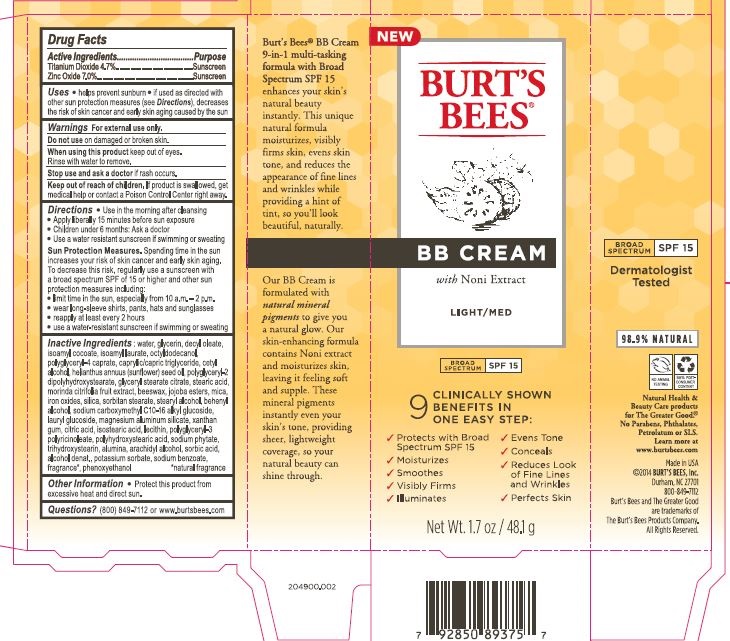 DRUG LABEL: BB Broad Spectrum SPF 15 Light to Medium
NDC: 26052-031 | Form: CREAM
Manufacturer: Burt's Bees
Category: otc | Type: HUMAN OTC DRUG LABEL
Date: 20241217

ACTIVE INGREDIENTS: TITANIUM DIOXIDE 4.7 g/100 g; ZINC OXIDE 7 g/100 g
INACTIVE INGREDIENTS: LECITHIN, SOYBEAN; POLYGLYCERYL-3 RICINOLEATE; SODIUM BENZOATE; TRICAPRIN; LAURYL GLUCOSIDE; OCTYLDODECANOL; GLYCERYL STEARATE CITRATE; DOCOSANOL; POTASSIUM SORBATE; DECYL OLEATE; POLYHYDROXYSTEARIC ACID (2300 MW); POLYGLYCERYL-4 CAPRATE; JOJOBA OIL; ALUMINUM OXIDE; ARACHIDYL ALCOHOL; SORBIC ACID; CITRIC ACID MONOHYDRATE; PHENOXYETHANOL; WATER; GLYCERIN; XANTHAN GUM; CETYL ALCOHOL; SORBITAN MONOSTEARATE; STEARYL ALCOHOL; SUNFLOWER OIL; TRIHYDROXYSTEARIN; MAGNESIUM ALUMINUM SILICATE; ISOSTEARIC ACID; ALCOHOL; PHYTATE SODIUM; SILICON DIOXIDE; YELLOW WAX; POLYGLYCERYL-2 DIPOLYHYDROXYSTEARATE; FERRIC OXIDE RED; ISOAMYL LAURATE; STEARIC ACID; MORINDA CITRIFOLIA FRUIT; MICA; ISOAMYL COCOATE

Active Ingredients

Titanium Dioxide 4.7%

Zinc Oxide 7.0%

PURPOSE

Sunscreen

Uses

- helps prevent sunburn
- if used as directed with other sun protection measures (see Directions), decreases the risk of skin cancer and early aging caused by the sun

Warnings

For external use only.

Do not use on damaged or broken skin.

When using this product keep out of eyes.

Rinse with water to remove.

Stop use and ask a doctor if rash occurs.

Keep Out of Reach of Children

If product is swallowed, get medical help or contact a Poison Control Center right away.

Directions

- Use in the morning after cleansing
- Apply liberally 15 minutes before sun exposure
- Children under 6 months: Ask a doctor
- Use a water resistent sunscreen if swimming or sweating

Sun Protection Measures. Spending time in the sun increases your risk of skin cancer and early aging. To decrease this risk, regularly use a sunscreen with a broad spectrum spf of 15 or higher and other sun protection measures including:

- limit time in ethe sun, especially from 10 a.m.- 2 p.m.
- wear long-sleeve shirts, pants, hats and sunglasses
- reapply at least every 2 hours
- use a water resistent sunscreen if swimming or sweating

INACTIVE INGREDIENT

Inactive Ingredients: water, glycerin, decyl oleate, isoamyl cocoate, isoamyl laurate, octyldodecanol, polyglyceryl-4 caprate, caprylic/capric triglyceride, cetyl alcohol, helianthus annuus (sunflower) seed oil, polyglyceryl-2 dipolyhydroxystearate, glyceryl stearate citrate, stearic acid, morinda citrifilia fruit extract, beeswax, jojoba esters, mica, iron oxides, silica, sorbitan stearate, stearyl alcohol, behenyl alcohol, sodium carboxymethyl C10-16 alkyl glucoside, lauryl glucoside, magnesium aluminum silicate, xanthan gum, citric acid, isostearic acid, lecithin, polyglyceryl-3polyricinoleate, polyhydroxysteric acid, sodium phytate, trihydroxystearin, alumina, arachidyl alcohol, sorbic acid, alcohol denat., potassium sorbate, sodium benzoate, fragrance*, phenoxyehtanol

*natural fragrance

Other Information:

- Protect this product from heat and direct sun.

Questions?

(800) 849-7112 or www.burtsbees.com

PACKAGE LABEL

Burt's Bees

BB Cream

with Noni Extract

LIGHT/MED

Broad Spectrum SPF 15

Net Wt 1.7 oz / 48.1g